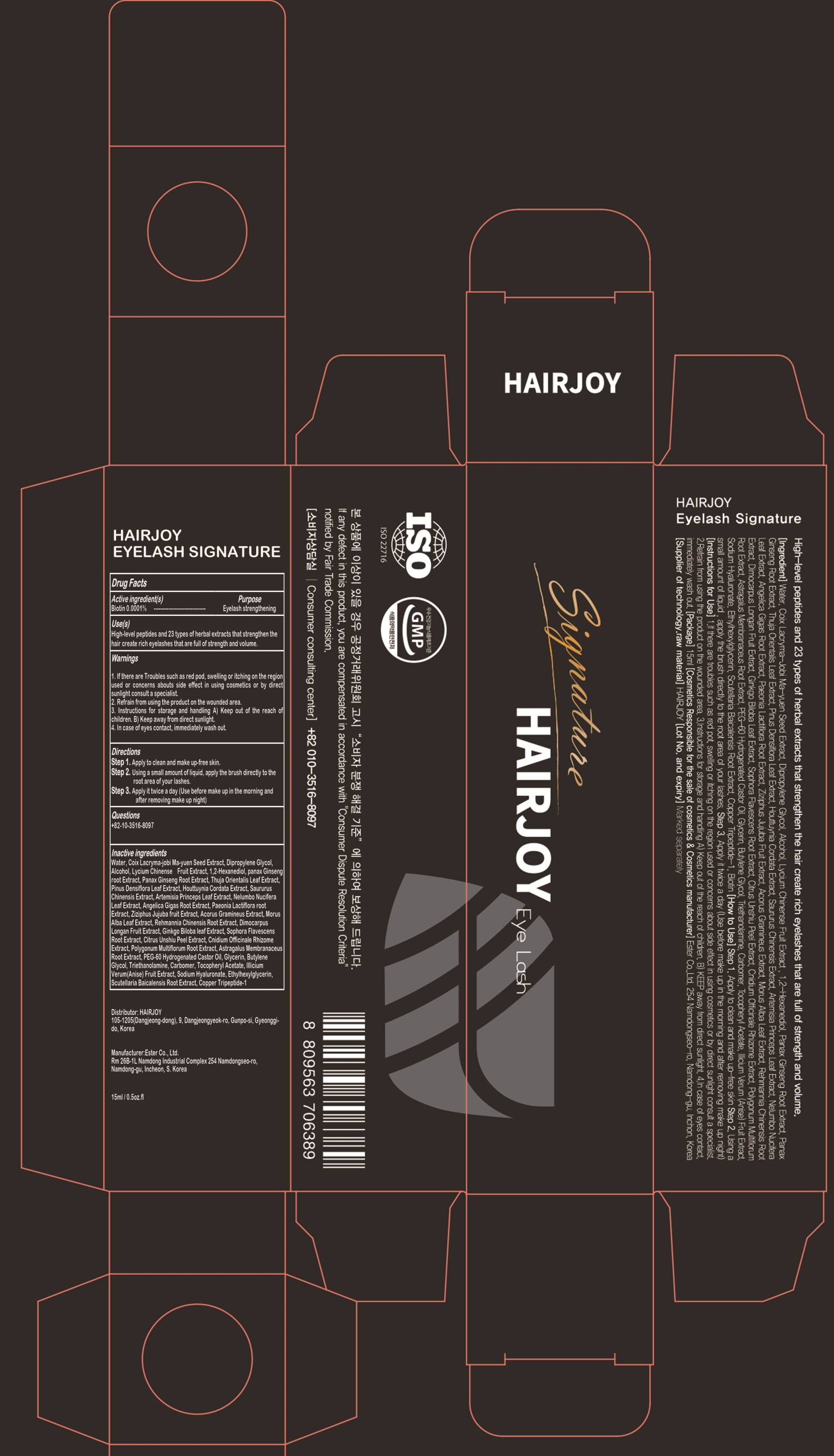 DRUG LABEL: HAIRJOY EYELASH SIGNATURE
NDC: 69384-080 | Form: LIQUID
Manufacturer: HAIRJOY
Category: otc | Type: HUMAN OTC DRUG LABEL
Date: 20201023

ACTIVE INGREDIENTS: Biotin 0.0001 g/100 mL
INACTIVE INGREDIENTS: Water; Dipropylene Glycol; Alcohol

ACTIVE INGREDIENT

Biotin 0.0001%

INACTIVE INGREDIENTS

Water, Coix Lacryma-jobi Ma-yuen Seed Extract, Dipropylene Glycol, Alcohol, Lycium Chinense Fruit Extract, 1,2-Hexanediol, panax Ginseng root Extract, Panax Ginseng Root Extract, Thuja Orientalis Leaf Extract, Pinus Densiflora Leaf Extract, Houttuynia Cordata Extract, Saururus Chinensis Extract, Artemisia Princeps Leaf Extract, Nelumbo Nucifera Leaf Extract, Angelica Gigas Root Extract, Paeonia Lactiflora root Extract, Ziziphus Jujuba fruit Extract, Acorus Gramineus Extract, Morus Alba Leaf Extract, Rehmannia Chinensis Root Extract, Dimocarpus Longan Fruit Extract, Ginkgo Biloba leaf Extract, Sophora Flavescens Root Extract, Citrus Unshiu Peel Extract, Cnidium Officinale Rhizome Extract, Polygonum Multiflorum Root Extract, Astragalus Membranaceus Root Extract, PEG-60 Hydrogenated Castor Oil, Glycerin, Butylene Glycol, Triethanolamine, Carbomer, Tocopheryl Acetate, Illicium Verum(Anise) Fruit Extract, Sodium Hyaluronate, Ethylhexylglycerin, Scutellaria Baicalensis Root Extract, Copper Tripeptide-1

PURPOSE

Eyelash strengthening

WARNINGS

1. If there are Troubles such as red pod, swelling or itching on the region used or concerns abouts side effect in using cosmetics or by direct sunlight consult a specialist.
2. Refrain from using the product on the wounded area.
3. Instructions for storage and handling A) Keep out of the reach of children. B) Keep away from direct sunlight.
4. In case of eyes contact, immediately wash out.

KEEP OUT OF REACH OF CHILDREN

Keep out of the reach of children

Uses

High-level peptides and 23 types of herbal extracts that strengthen the hair create rich eyelashes that are full of strength and volume.

Directions

Step 1. Apply to clean and make up-free skin.
Step 2. Using a small amount of liquid, apply the brush directly to the root area of your lashes.
Step 3. Apply it twice a day (Use before make up in the morning and after removing make up night)

QUESTIONS

+82-10-3516-8097